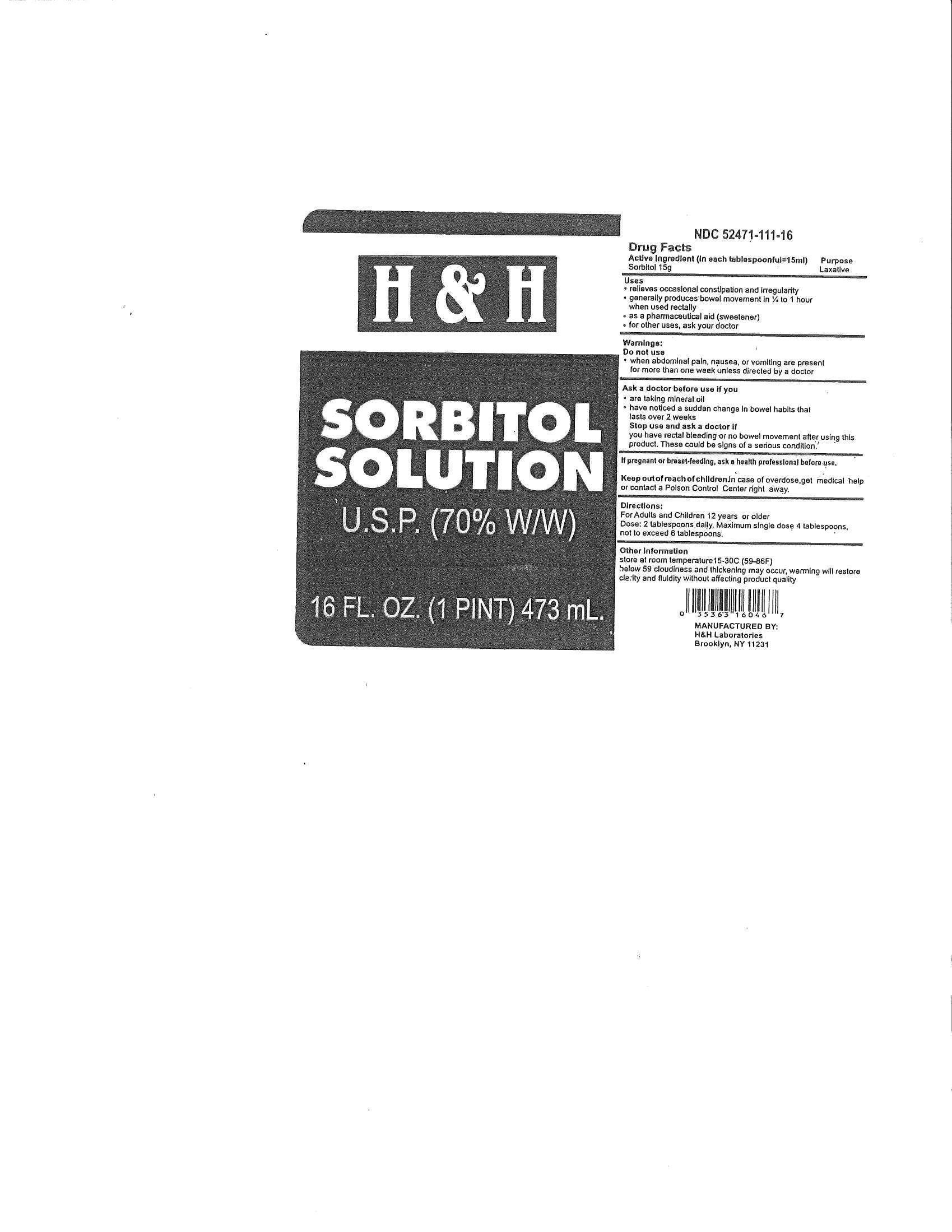 DRUG LABEL: Sorbitol
NDC: 52471-111 | Form: SOLUTION
Manufacturer: H&H Laboratories, Inc.
Category: otc | Type: HUMAN OTC DRUG LABEL
Date: 20130610

ACTIVE INGREDIENTS: SORBITOL 1 g/1 mL
INACTIVE INGREDIENTS: WATER

DRUG FACTS

Active Ingredient in each tablespoon=15 ml Sorbitol 15gm

Purpose-Laxative

INDICATIONS AND USAGE

Uses-Relieves occasional constipation and irregularity. Generally produces bowel movement in 1/4 to 1 hour when used rectally. As a pharmaceutical aid (sweetener). For other uses, ask your doctor.

DOSAGE AND ADMINISTRATION

Directions: For adults and children 12 years or older: Dose-2 tablespoons. maximum single dose-4 tablespoons. Not to exceed 6 tablespoons daily

Keep out of reach of children. In case of overdose, get medical help or contact a Poison Control Center right away.

WARNINGS

Warnings: Do not use: When abdominal pain, nausea, or vomiting are present for more than a week unless directed by a doctor.

Ask a doctor before use if you-are taking mineral oil, have noticed a sudden change in bowel habi9ts that lasts over 2 weeks.

Stop use and ask a doctor if: Youn have rectal bleeding or no bowel movement after using this product. These could be signs of a serious condition.

Inactive Ingredients: Purified Water

PACKAGE LABEL

MM1